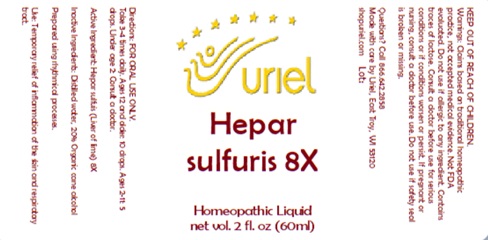 DRUG LABEL: Hepar sulfuris 8X
NDC: 48951-5147 | Form: LIQUID
Manufacturer: Uriel Pharmacy, Inc
Category: homeopathic | Type: HUMAN OTC DRUG LABEL
Date: 20250819

ACTIVE INGREDIENTS: CALCIUM SULFIDE 8 [hp_X]/1 mL
INACTIVE INGREDIENTS: WATER; ALCOHOL

Hepar sulfuris 8X

INDICATIONS AND USAGE

Directions: FOR ORAL USE ONLY.

DOSAGE AND ADMINISTRATION

Take 3-4 times daily. Ages 12 and older: 10 drops. Ages 2-11: 5 drops. Under age 2: Consult a doctor.

Active Ingredient: Hepar sulfuis (Liver of lime) 8X

Inactive Ingredients: Distilled water, 20% Organic cane alcohol

Prepared using rhythmical processes.

PURPOSE

Use: Temporary relief of inflammation of the skin and respiratory tract.

KEEP OUT OF REACH OF CHILDREN.

WARNINGS

Warnings: Claims based on traditional homeopathic practice, not accepted medical evidence. Not FDA evaluated. Do not use if allergic to any ingredient. Contains traces of lactose. Consult a doctor before use for serious conditions or if conditions worsen or persist. If pregnant or nursing, consult a doctor before use. Do not use if safety seal is broken or missing.

Questions? Call 866.642.2858
Made with care by Uriel, East Troy, WI 53120
shopuriel.com Lot: